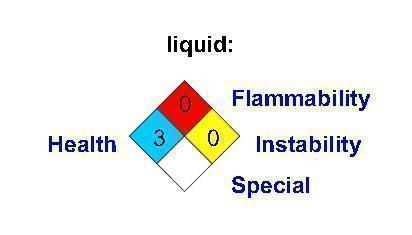 DRUG LABEL: Carbon Dioxide
NDC: 63917-001 | Form: GAS
Manufacturer: Airgas Carbonic, Inc.
Category: prescription | Type: HUMAN PRESCRIPTION DRUG LABEL
Date: 20140217

ACTIVE INGREDIENTS: Carbon Dioxide 1000 mL/1 L

Carbon Dioxide

PACKAGE LABEL

Carbon Dioxide

Liquid: 3 0 0

Health, Flammability, Instability, Special